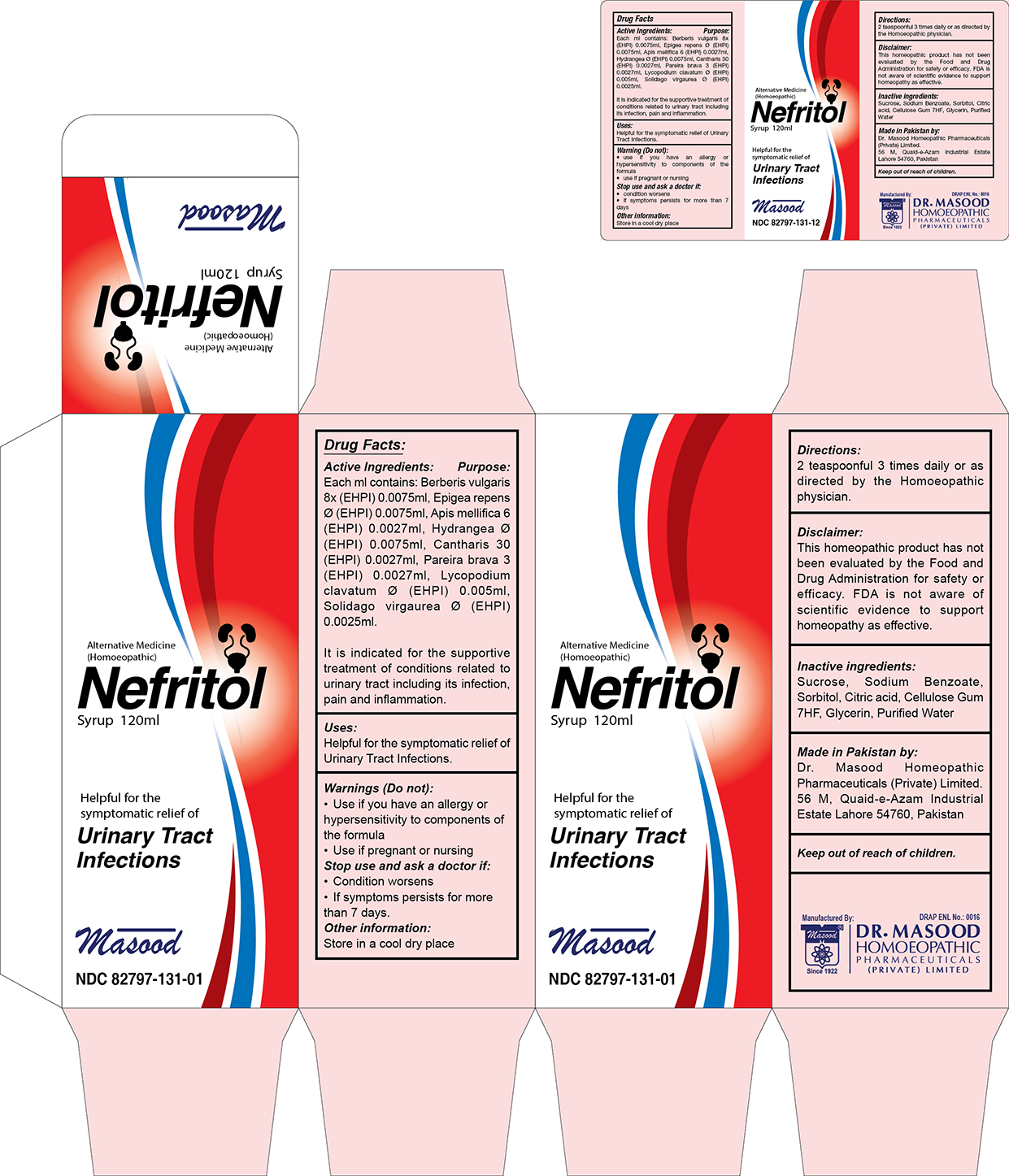 DRUG LABEL: Nefritol syrup
NDC: 82797-131 | Form: SYRUP
Manufacturer: Dr. Masood Homeopathic Pharmaceuticals Private Limited
Category: homeopathic | Type: HUMAN OTC DRUG LABEL
Date: 20250422

ACTIVE INGREDIENTS: CHONDRODENDRON TOMENTOSUM ROOT 0.0027 mg/120 mL; HYDRANGEA ARBORESCENS WHOLE 0.0075 mg/120 mL; EPIGAEA REPENS 0.0075 mg/120 mL; APIS MELLIFERA 0.0027 mg/120 mL; BERBERIS VULGARIS WHOLE 0.0075 mg/120 mL; LYTTA VESICATORIA 0.0027 mg/120 mL; SOLIDAGO VIRGAUREA WHOLE 0.0025 mg/120 mL; LYCOPODIUM CLAVATUM WHOLE 0.005 mg/120 mL
INACTIVE INGREDIENTS: GLYCERIN 1 mL/120 mL; SORBITOL SOLUTION 70% 2 mL/120 mL; SODIUM BENZOATE 0.0066 g/120 mL; SODIUM SACCHARIN 0.0012 g/120 mL; WATER 120 mL/120 mL; CELLULOSE GUM 0.007 g/120 mL

Indications and Usage

it is indicated for the supportive treatment of conditions related to urinary tract including its infections, pain and inflammation

Inactive Ingredients

Sodium Benzoate

Sodium Saccharine

Cellulose Gum

Glycerin

Sorbotol 70%

Water

Active Ingredients

Berberis Vulgaris

Epigaea repens

Apis mellifica

Hydrangea arborescens

Cantharis

Pareira brava

Lycopodium clavatum

Solidago virgaurea

Purpose

Ingredients Purpose

Berberis vulgaris used for urinary tract problems like calculi and infections

Epigaea repens used in Chronic cystitis with dysuria

Apis mellifica helps treat Inflammation of kidney, Burning and soreness when urinating

Hydrangea arborescens Traets Renal colic

Cantharis Helps overcome burning micturation

Pareira brava Useful in renal colic, prostatic affection and catarrh of bladder

Lycopodium clavatum useful in Urinary disturbances

Solidago virgaurea Helps in renal cloic with dysuria

Warnings

Do not:

- use if you have an allergy or hypersensitivity to components of the formula
- use if pregnant or nursing

Stop use and ask a doctor if:

- condition worsens
- If symptoms persists for more than 7 days

Keep out of reach of children.

Keep out of the reach of children

Keep this and all medicines out of the reach of children

Dosage and Administartion

2 teaspoonful 3 times a day or as directed by licensed homeopathic practitioner